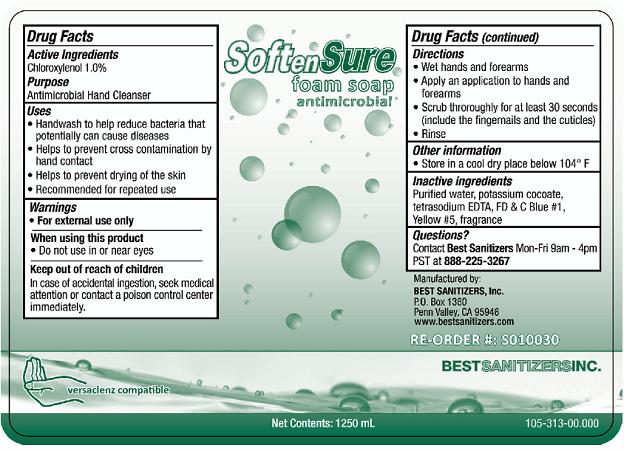 DRUG LABEL: Soften Sure Foam Antimicrobial
NDC: 59900-211 | Form: LIQUID
Manufacturer: Best Sanitizers, Inc
Category: otc | Type: HUMAN OTC DRUG LABEL
Date: 20241205

ACTIVE INGREDIENTS: CHLOROXYLENOL 10 g/1000 mL
INACTIVE INGREDIENTS: WATER; POTASSIUM COCOATE; EDETATE SODIUM; FD&C BLUE NO. 1; FD&C YELLOW NO. 5

Soften Sure Foam Antimicrobial 59900-211

Active Ingredient

Chloroxylenol 1.0%

Purpose

Antimicrobial Hand Cleanser

Uses

- Handwash to help reduce bacteria that potentially can cause diseases
- Helps to prevent cross contaminiation by hand contact
- Helps to prevent drying of the skin
- Recommended for repeated use

Warnings

- For external use only

When Using this product

- Do not use in or near eyes.

Keep out of reach of children

In case of accidental ingestion seek medical attention or contact a poison center immediately.

Directions

- Wet hands and forearms
- Apply an application to hands and forearms
- Scrub thoroughly for at least 30 seconds (include the fingernails and the cuticles)
- Rinse

Other Information

- Store in a cool dry place below 104° F

Inactive ingredients

purified water, potassium cocoate, tetrasodium EDTA, FDC No. 1, Yellow No.5, fragrance

Questions?

Contact Best SanitizersMon-Fri 9am - 4pm PST at 888-225-3267

PACKAGE LABEL

NDC 59900-211-06

NDC 59900-211-10

NDC 59900-211-11

Soften Sure Foam Soap antimicrobial